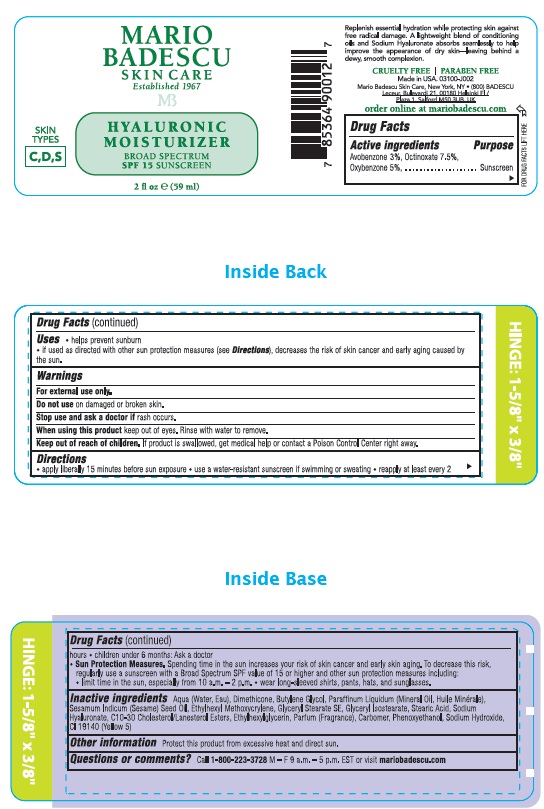 DRUG LABEL: Hyaluronic Moisturizer
NDC: 54111-182 | Form: CREAM
Manufacturer: Bentley Laboratories LLC
Category: otc | Type: HUMAN OTC DRUG LABEL
Date: 20241016

ACTIVE INGREDIENTS: OCTINOXATE 7.5 g/100 mL; OXYBENZONE 5.0 g/100 mL; AVOBENZONE 3.0 g/100 mL
INACTIVE INGREDIENTS: WATER; DIMETHICONE; BUTYLENE GLYCOL; MINERAL OIL; SESAME OIL; ETHYLHEXYL METHOXYCRYLENE; GLYCERYL STEARATE SE; GLYCERYL ISOSTEARATE; STEARIC ACID; HYALURONATE SODIUM; C10-30 CHOLESTEROL/LANOSTEROL ESTERS; ETHYLHEXYLGLYCERIN; CARBOMER HOMOPOLYMER, UNSPECIFIED TYPE; PHENOXYETHANOL; SODIUM HYDROXIDE; FD&C YELLOW NO. 5

MARIO BADESCU HYALURONIC MOISTURIZER BROAD SPECTRUM SPF 15 SUNSCREEN

Drug Facts

Active ingredients

Avobenzone 3%, Octinoxate 7.5%, Oxybenzone 5%

Purpose

Sunscreen

INDICATIONS AND USAGE

Uses ● helps prevent sunburn
● If used as directed with other sun protection measures (see Directions),

decreases the risk of skin cancer and early aging caused by the sun.

Warnings

For external use only.

Do not use on damaged or broken skin.

Stop use and ask a doctor if rash occurs.

• When using this product keep out of eyes. Rinse with water to remove.

Keep out of reach of children.

If product is swallowed, get medical help or contact a Poison Control Center right away.

Directions
•apply liberally 15 minutes before sun exposure • use a water-resistant sunscreen if swimming or sweating •reapply at least every 2 hours
• children under 6 months: Ask a doctor •Sun Protection Measures. Spending time in the sun increases your risk of skin cancer and early aging. To decrease this risk, regularly use a sunscreen with a Broad Spectrum SPF value of 15 or higher and other sun protection measur es including:
• limit time in the sun, especially from 10 a.m. - 2 p.m. • Wear long-sleeved shirts, pants, hats, and sunglasses.

INACTIVE INGREDIENT

Inactive Ingredients Aqua (Water, Eau), Dimethicone, Butylene Glycol, Paraffinum Liquidum (Mineralil, Huile Minerale)
Sesamum Indicum (Sesame) Seed Oil, Ethylhexyl Methoxycrylene, Glyceryl Stearate SE, Glyceryl Isostearate, Stearic Acid, Sodium
Hyaluronate, C 10-30 Cholesterol/Lanosterol Esters, Ethylhexylglycerin, Parfum (Fragrance), Carbomer, Phenoxyethanol, Sodium Hydroxide, Yellow 5 (CI 19140)

Other information Protect this product from excessive heat and direct sun,

Questions or comments?Call 1-800-223-3728 M – F 9 a.m. – 5 p.m. EST or visit mariobadescu.com

Mario Badescu HYALURONIC MOISTURIZER SPF 15 product label

MARIO
BADESCU
SKIN CARE
Established 1967
MB

HYALURONIC MOISTURIZER

Store in a cool, dry place. 0001
Manufactured in the US with
globally-sourced ingredients.
Mario Badescu Skin Care,
New York, NY • (800) BADESCU
Leceur, Bulevardi 21, 00180
Helsinki FI / Plaza 1, Salford
M50 3UB, UK

order online at
mariobadescu.com

res